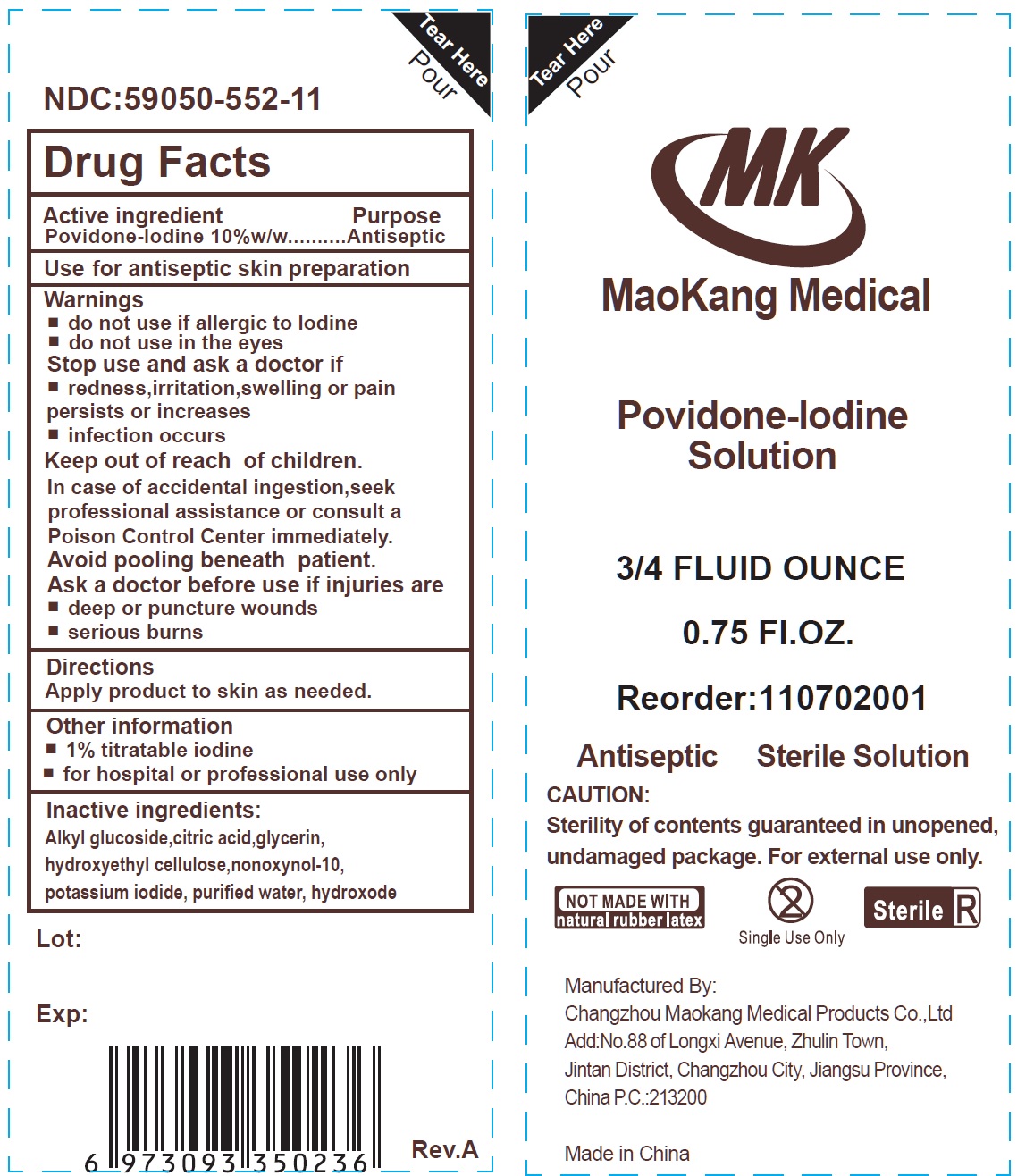 DRUG LABEL: sterile
NDC: 59050-552 | Form: PATCH
Manufacturer: Changzhou Maokang Medical Products Co., Ltd
Category: otc | Type: HUMAN OTC DRUG LABEL
Date: 20241121

ACTIVE INGREDIENTS: POVIDONE-IODINE 10 g/100 g
INACTIVE INGREDIENTS: CITRIC ACID MONOHYDRATE; GLYCERIN; HYDROXYETHYL CELLULOSE, UNSPECIFIED; NONOXYNOL-10; POTASSIUM IODIDE; WATER

Povidone-Iodine Solution, sterile

Active ingredient

Povidone-lodine 10%w/w

Purpose

Antiseptic

Use

for antiseptic skin preparation

Warnings

do not use

- if allergic to lodine
- do not use in the eyes

Stop use and ask a doctor if

- redness, irritation, swelling or pain persists or increases
- infection occurs

Keep out of reach of children.

In case of accidental ingestion, seek professional assistance or consult a Poison Control Center immediately.

Avoid pooling beneath patient.

Ask a doctor before use if injuries are

- deep or puncture wounds
- serious burns

Driections

Apply product to skin as needed.

Other information

- 1% titratable iodine
- for hospital or professional use only

Inactive ingredients:

Alkyl glucoside,citric acid,glycerin, hydroxyethyl cellulose,nonoxynol-10, potassium iodide, purified water, hydroxode